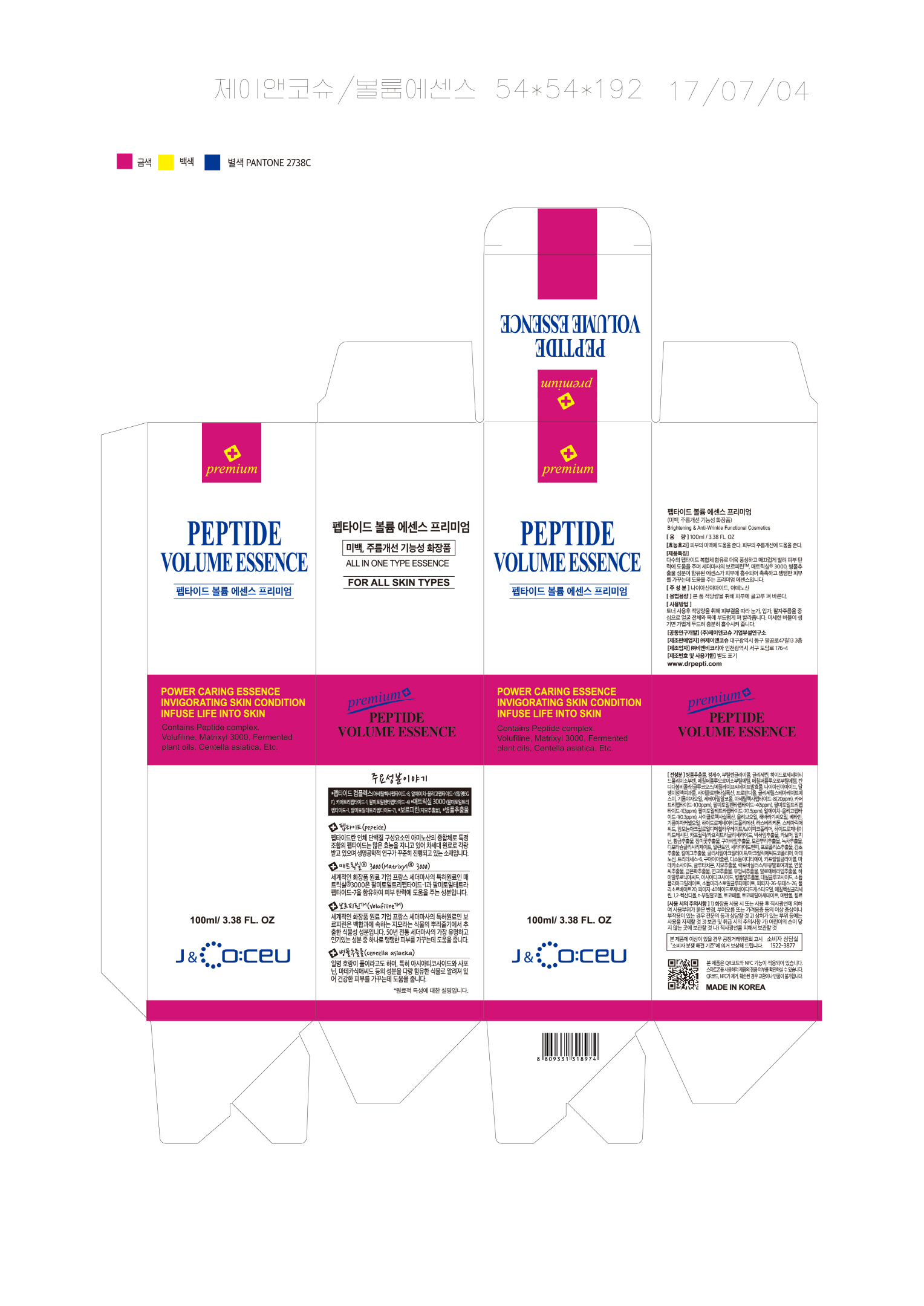 DRUG LABEL: PEPTIDE VOLUME ESSENCE PREMIUM
NDC: 71146-0003 | Form: CREAM
Manufacturer: J&COCEU Co Ltd
Category: otc | Type: HUMAN OTC DRUG LABEL
Date: 20170822

ACTIVE INGREDIENTS: NIACINAMIDE 2 g/100 mL; ADENOSINE 0.04 g/100 mL
INACTIVE INGREDIENTS: WATER; BUTYLENE GLYCOL; GLYCERIN

Drug Facts

ACTIVE INGREDIENT

Niacinamide, Adenosine

INACTIVE INGREDIENT

Glycerin, Water, Butylene Glycol, etc.

PURPOSE

whitening
anti wrinkle

INDICATIONS AND USAGE

After applying a generous, even layer to skin.

If bubble up, Pat it lightly on your skin to absorb.

keep out of reach of the children

WARNINGS

1) See you doctor if the first sign occurs like mild redness, rash, or any allergic reactions.

2) Do not apply on scars or infection areas.

3) Storage:

Keep out of reach of children

Keep in a dry and dark place.

DOSAGE AND ADMINISTRATION

for external use only